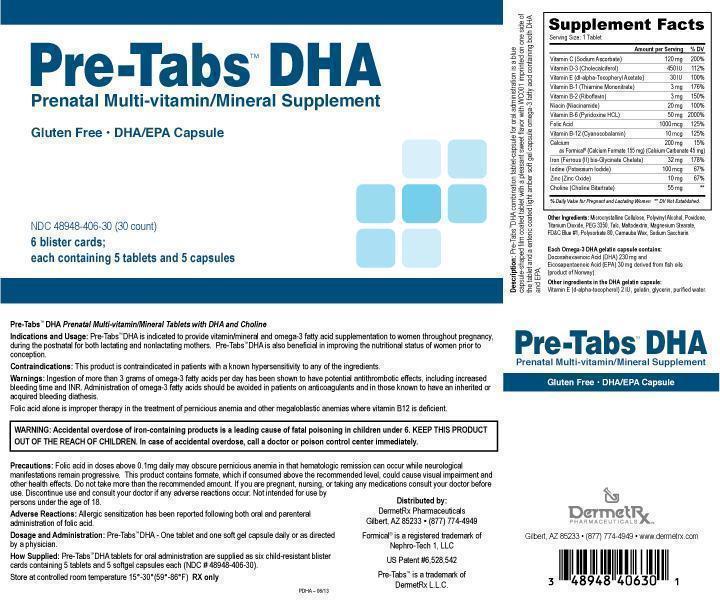 DRUG LABEL: Pre-Tabs DHA
NDC: 48948-406 | Form: KIT | Route: ORAL
Manufacturer: DEREMETRX LLC
Category: prescription | Type: HUMAN PRESCRIPTION DRUG LABEL
Date: 20130915

ACTIVE INGREDIENTS: SODIUM ASCORBATE 120 mg/1 1; CHOLECALCIFEROL 450 [iU]/1 1; TOCOPHERSOLAN 30 [iU]/1 1; THIAMINE MONONITRATE 3 mg/1 1; RIBOFLAVIN 3 mg/1 1; NIACINAMIDE 20 mg/1 1; PYRIDOXINE HYDROCHLORIDE 50 mg/1 1; FOLIC ACID 1 mg/1 1; CYANOCOBALAMIN 10 ug/1 1; CALCIUM FORMATE 155 mg/1 1; CALCIUM CARBONATE 45 mg/1 1; FERROUS BISGLYCINATE 32 mg/1 1; POTASSIUM IODIDE 100 ug/1 1; ZINC OXIDE 10 mg/1 1; CHOLINE BITARTRATE 55 mg/1 1; DOCONEXENT 230 mg/1 1; ICOSAPENT 30 mg/1 1; ALPHA-TOCOPHEROL, D- 2 [iU]/1 1
INACTIVE INGREDIENTS: CELLULOSE, MICROCRYSTALLINE; POLYVINYL ALCOHOL; POVIDONE; TITANIUM DIOXIDE; POLYETHYLENE GLYCOL 3350; TALC; MALTODEXTRIN; FD&C BLUE NO. 1; POLYSORBATE 80; CARNAUBA WAX; SACCHARIN SODIUM; GELATIN; GLYCERIN; WATER

Pre-Tabs DHA Prenatal Multi-vitamin/Mineral Tablet

DESCRIPTION

Descripton: Pre-Tabs DHA combination tablet-capsule for oral administration is a light blue capsule-shaped film coated tablet with a pleasant sweet flavor with WC001 imprinted on one side of the tablet and a light amber soft gel capsule omega-3 fatty acid containing both DHA and EPA.

Indications and Usage: Pre-Tabs DHA is indicated to provide vitamin/mineral and omega-3 fatty acid supplementation to women throughout pregnancy, during the postnatal for both lactating and nonlactating mothers. Pre-Tabs DHA is also beneficial in improving the nutritional status of women prior to conception.

CONTRAINDICATIONS

Contraindications: This product is contraindicated in patients with a known hypersensitivity to any of the ingredients .

WARNINGS

Warnings: Ingestion of more than 3 grams of omega-fatty acids per day has been shown to have potential antithrombotic effects, including increased bleeding time and INR. Administration of omega-3 fatty acids should be avoided in patients on anticoagulants and in those known to have an inherited or acquired bleeding diathesis. Folic acid alone is improper therapy in the treatment of pernicious anemia and other megaloblastic anemias where vitamin B12 is deficient.

WARNINGS

Warnings: Folic acid alone is improper therapy in the treatment of pernicious anemia and other megaloblastic anemias where B12 is deficient.

BOXED WARNING

WARNING: Accidental overdose of iron-containing products is a leading cause of fatal poisoning in children under 6. KEEP THIS PRODUCT OUT OF THE REACH OF CHILDREN. In case of accidental overdose, call a doctor or poison control center immediately.

PRECAUTIONS

Precautions: Folic acid in doses above 0.1mg daily may obscure pernicious anemia in that hematologic remission can occur while neurological manifestations remain progressive. This product contains formate, which if consumed above the recommended level, could cause visual impairment and other health effects. Do not take more than the recommended amount. If you are pregnant, nursing, or taking any medications consult your doctor before use. Discontinue use and consult your doctor if any adverse reactions occur. Not intended for use by persons under the age of 18.

ADVERSE REACTIONS

Adverse Reactions: Allergic sensitization has been reported following both oral and parenteral administration of folic acid.

Dosage and Administration: Pre-Tabs DHA - One tablet and one soft gel capsule daily or as directed by a physician.

HOW SUPPLIED

How Supplied: Pre-Tabs DHA tablets for oral administration are supplied as six child-resistant blister cards containing 5 tablets and 5 softgel capsules each (NDC# 48648-406-30).

PACKAGE LABEL

Pre-Tabs DHA

Prenatal Multi-vitamin/Mineral Supplement

Gluten Free

NDC 48948-406-30 (30 count)

6 blister cards

each containing 5 tablets and 5 capsules

877-774-4949

www.dermetrx.com